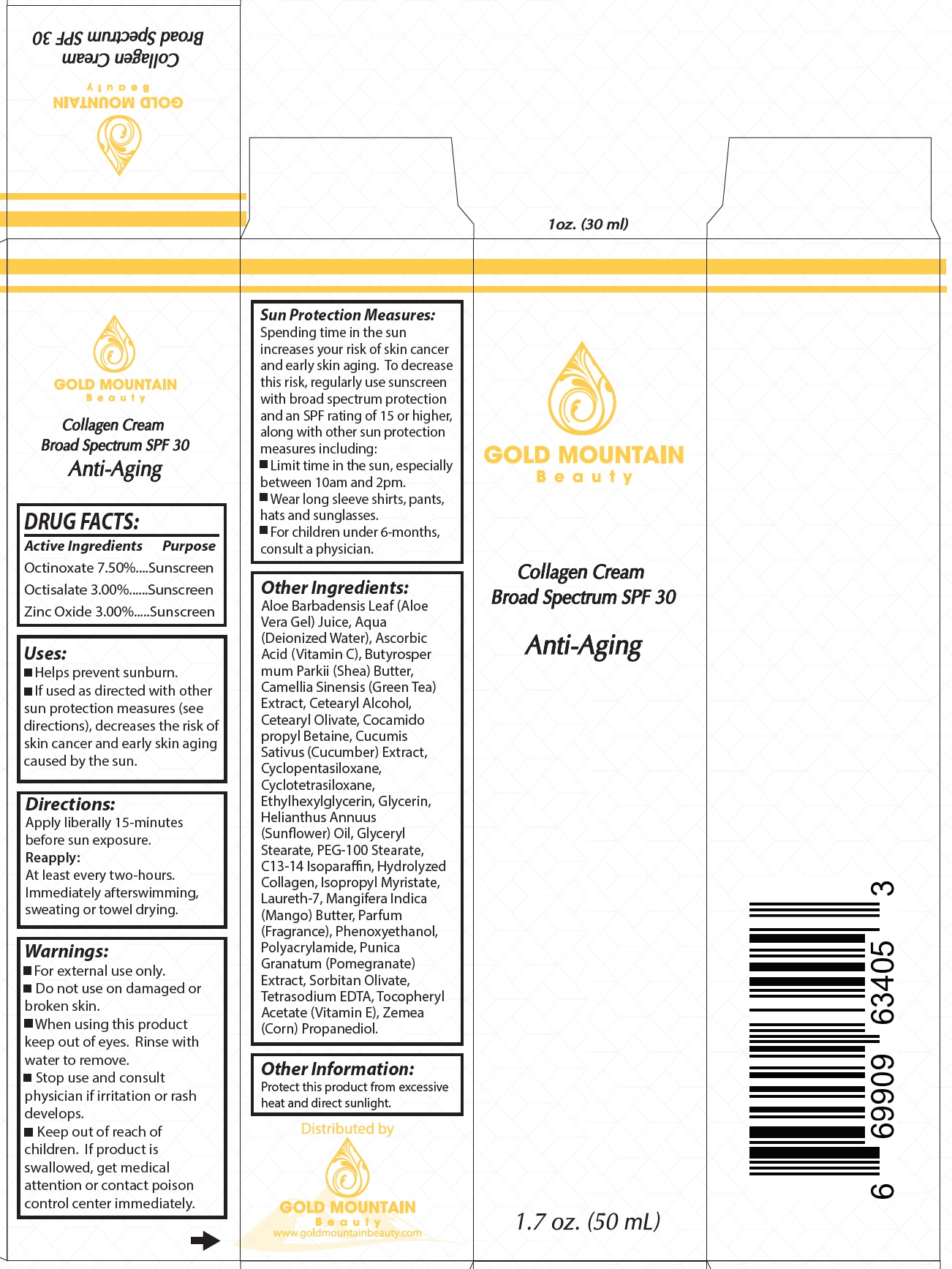 DRUG LABEL: GOLD MOUNTAIN BEAUTY Collagen Broad Spectrum SPF 30
NDC: 79214-157 | Form: CREAM
Manufacturer: TT Fitness, Inc
Category: otc | Type: HUMAN OTC DRUG LABEL
Date: 20231106

ACTIVE INGREDIENTS: OCTINOXATE 75 mg/1 mL; OCTISALATE 30 mg/1 mL; ZINC OXIDE 30 mg/1 mL
INACTIVE INGREDIENTS: ALOE VERA LEAF; WATER; ASCORBIC ACID; GREEN TEA LEAF; CETOSTEARYL ALCOHOL; CETEARYL OLIVATE; COCAMIDOPROPYL BETAINE; CUCUMBER; CYCLOMETHICONE 5; CYCLOMETHICONE 4; ETHYLHEXYLGLYCERIN; GLYCERIN; HELIANTHUS ANNUUS FLOWERING TOP; GLYCERYL MONOSTEARATE; PEG-100 STEARATE; C13-14 ISOPARAFFIN; ISOPROPYL MYRISTATE; LAURETH-7; MANGO; PHENOXYETHANOL; POMEGRANATE; SORBITAN OLIVATE; EDETATE SODIUM; .ALPHA.-TOCOPHEROL ACETATE; CORN; PROPANEDIOL

GOLD MOUNTAIN BEAUTY Collagen Cream Broad Spectrum SPF-30

Active Ingredients

Octinoxate 7.50%

Octisalate 3.00%

Zinc Oxide 3.00%

Purpose

Sunscreen

Uses:

- Helps prevent sunburn.
- If used as directed with other sun protection measures (see directions), decreases the risk of skin cancer and early skin aging caused by the sun.

Directions:

Apply liberally 15-minutes before sun exposure. At least every two-hours. Immediately afterswimming, sweating or towel drying.
Reapply:

Spending time in the sun increases your risk of skin cancerand early skin aging. To decrease this risk, regularly use sunscreen with broad spectrum protection and an SPF rating of 15 or higher, along with other sun protection measures including: Sun Protection Measures:

- Limit time in the sun, especially between 10am and 2pm.
- Wear long sleeve shirts, pants, hats and sunglasses.
- For children under 6-months, consult a physician.

Warnings:

For external use only.

Do not use

- on damaged or broken skin.

When using this product

- keep out of eyes. Rinse with water to remove.

Stop use and consult physician

if irritation or rash develops.

Keep out of reach of children.

If product is swallowed, get medical attention or contact poison control center immediately.

Other Ingredients:

Aloe Barbadensis Leaf (Aloe Vera Gel) Juice, Aqua (Deionized Water), Ascorbic Acid (Vitamin C), Butyrosper mum Parkii (Shea) Butter,Camellia Sinensis (Green Tea) Extract, Cetearyl Alcohol, Cetearyl Olivate, Cocamido propyl Betaine, Cucumis Sativus (Cucumber) Extract, Cyclopentasiloxane, Cyclotetrasiloxane, Ethylhexylglycerin, Glycerin, Helianthus Annuus (sunflower) Oil, Glyceryl Stearate, PEG-100 Stearate, C13-14 Isoparaffin, Hydrolyzed Collagen, Isopropyl Myristate, Laureth-7, Mangifera Indica (Mango) Butter, Parfum (Fragrance), Phenoxyethanol, Polyacrylamide, Punica Granatum (Pomegranate) Extract, Sorbitan Olivate, Tetrasodium EDTA, Tocopheryl Acetate (Vitamin E), Zemea (Corn) Propanediol.

Other Information:

Protect this product from excessive heat and direct sunlight.